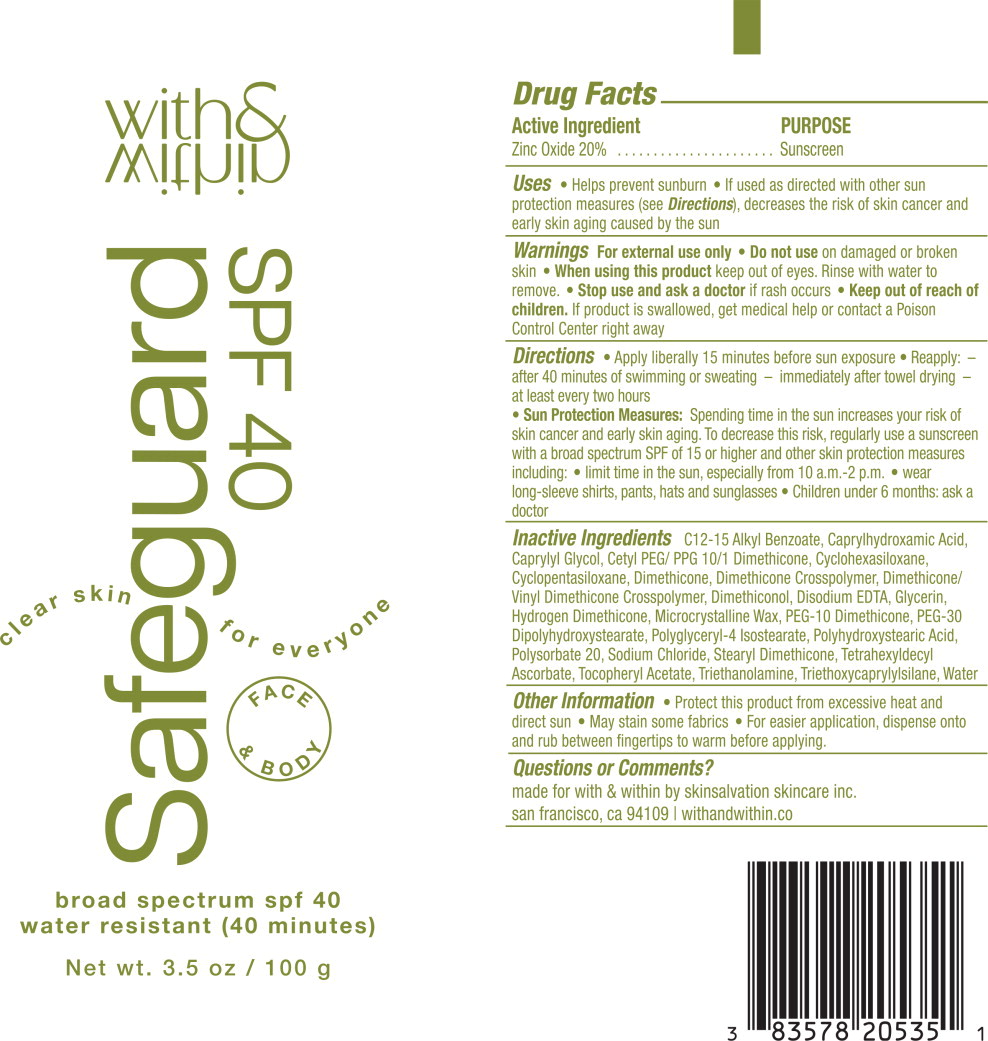 DRUG LABEL: Safeguard SPF 40
NDC: 83578-205 | Form: CREAM
Manufacturer: Skinsalvation Skincare, Inc.
Category: otc | Type: HUMAN OTC DRUG LABEL
Date: 20230714

ACTIVE INGREDIENTS: Zinc Oxide 200 mg/1 g
INACTIVE INGREDIENTS: ALKYL (C12-15) BENZOATE; CAPRYLHYDROXAMIC ACID; CAPRYLYL GLYCOL; CETYL PEG/PPG-10/1 DIMETHICONE (HLB 5); CYCLOMETHICONE 6; CYCLOMETHICONE 5; DIMETHICONE 100; DIMETHICONE CROSSPOLYMER (450000 MPA.S AT 12% IN CYCLOPENTASILOXANE); DIMETHICONE/VINYL DIMETHICONE CROSSPOLYMER (SOFT PARTICLE); DIMETHICONOL (2000 CST); EDETATE DISODIUM; GLYCERIN; HYDROGEN DIMETHICONE (20 CST); MICROCRYSTALLINE WAX; PEG-10 DIMETHICONE (600 CST); PEG-30 DIPOLYHYDROXYSTEARATE (4000 MW); POLYGLYCERYL-4 ISOSTEARATE; POLYHYDROXYSTEARIC ACID (2300 MW); POLYSORBATE 20; SODIUM CHLORIDE; STEARYL DIMETHICONE (400 MPA.S AT 50C); TETRAHEXYLDECYL ASCORBATE; .ALPHA.-TOCOPHEROL ACETATE; TROLAMINE; TRIETHOXYCAPRYLYLSILANE; WATER

Drug Facts

Active Ingredient

Zinc Oxide 20%

PURPOSE

Sunscreen

Uses

- Helps prevent sunburn
- If used as directed with other sun protection measures (see Directions), decreases the risk of skin cancer and early skin aging caused by the sun

Warnings

For external use only

- Do not use on damaged or broken skin

- When using this product keep out of eyes. Rinse with water to remove.

- Stop use and ask a doctor if rash occurs

- Keep out of reach of children. If product is swallowed, get medical help or contact a Poison Control Center right away

Directions

- Apply liberally 15 minutes before sun exposure
- Reapply: - after 40 minutes of swimming or sweating - immediately after towel drying - at least every two hours
- Sun Protection Measures: Spending time in the sun increases your risk of skin cancer and early skin aging. To decrease this risk, regularly use a sunscreen with a broad spectrum SPF of 15 or higher and other skin protection measures including:
  - limit time in the sun, especially from 10 a.m.-2 p.m.
  - wear long-sleeve shirts, pants, hats and sunglasses
- Children under 6 months: ask a doctor

Inactive Ingredients

C12-15 Alkyl Benzoate, Caprylhydroxamic Acid, Caprylyl Glycol, Cetyl PEG/ PPG 10/1 Dimethicone, Cyclohexasiloxane, Cyclopentasiloxane, Dimethicone, Dimethicone Crosspolymer, Dimethicone/ Vinyl Dimethicone Crosspolymer, Dimethiconol, Disodium EDTA, Glycerin, Hydrogen Dimethicone, Microcrystalline Wax, PEG-10 Dimethicone, PEG-30 Dipolyhydroxystearate, Polyglyceryl-4 Isostearate, Polyhydroxystearic Acid, Polysorbate 20, Sodium Chloride, Stearyl Dimethicone, Tetrahexyldecyl Ascorbate, Tocopheryl Acetate, Triethanolamine, Triethoxycaprylylsilane, Water

Other Information

- Protect this product from excessive heat and direct sun
- May stain some fabrics
- For easier application, dispense onto and rub between fingertips to warm before applying.

Questions or Comments?

made for with & within by skinsalvation skincare inc.

san francisco, ca 94109 | withandwithin.co

Principal Display Panel – 100 g Tube Label

with &
within

safeguard
SPF 40

clear skin for everyone

FACE
& BODY

broad spectrum spf 40

water resistant (40 minutes)

Net wt. 3.5 oz / 100 g